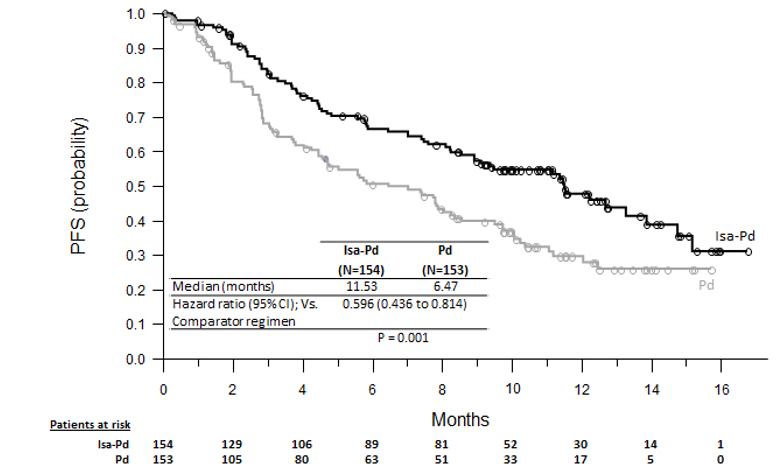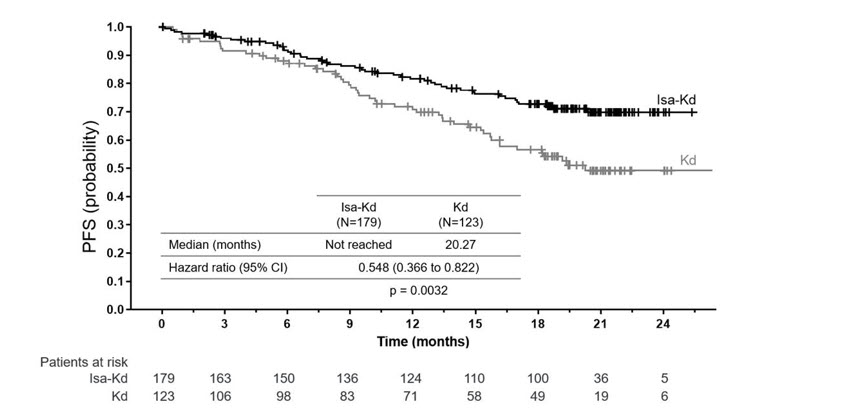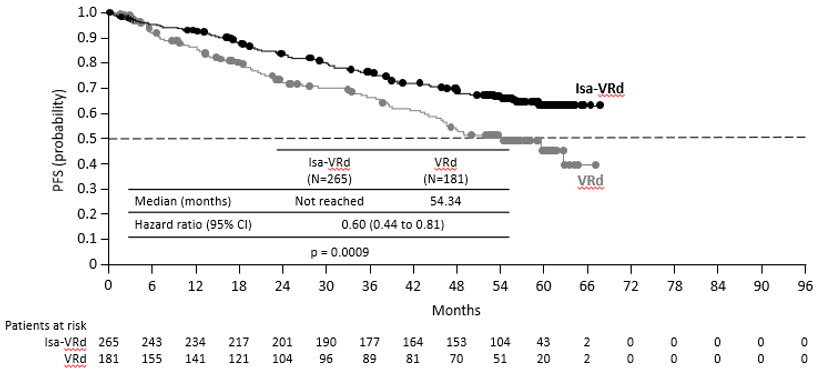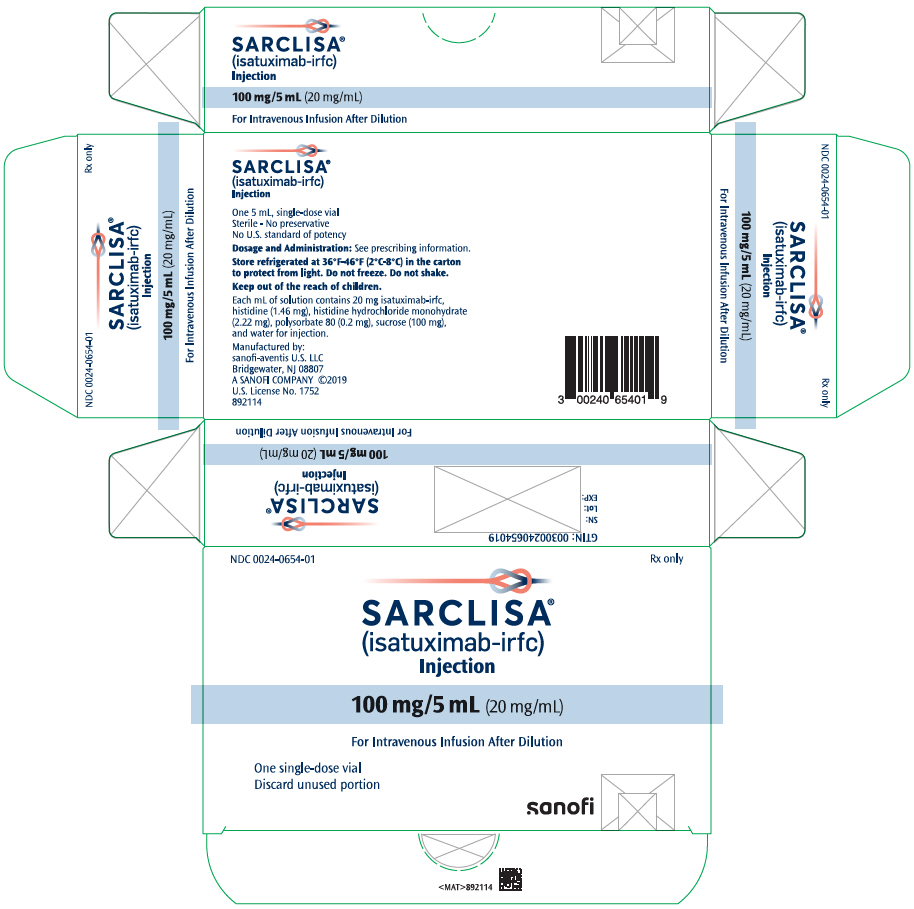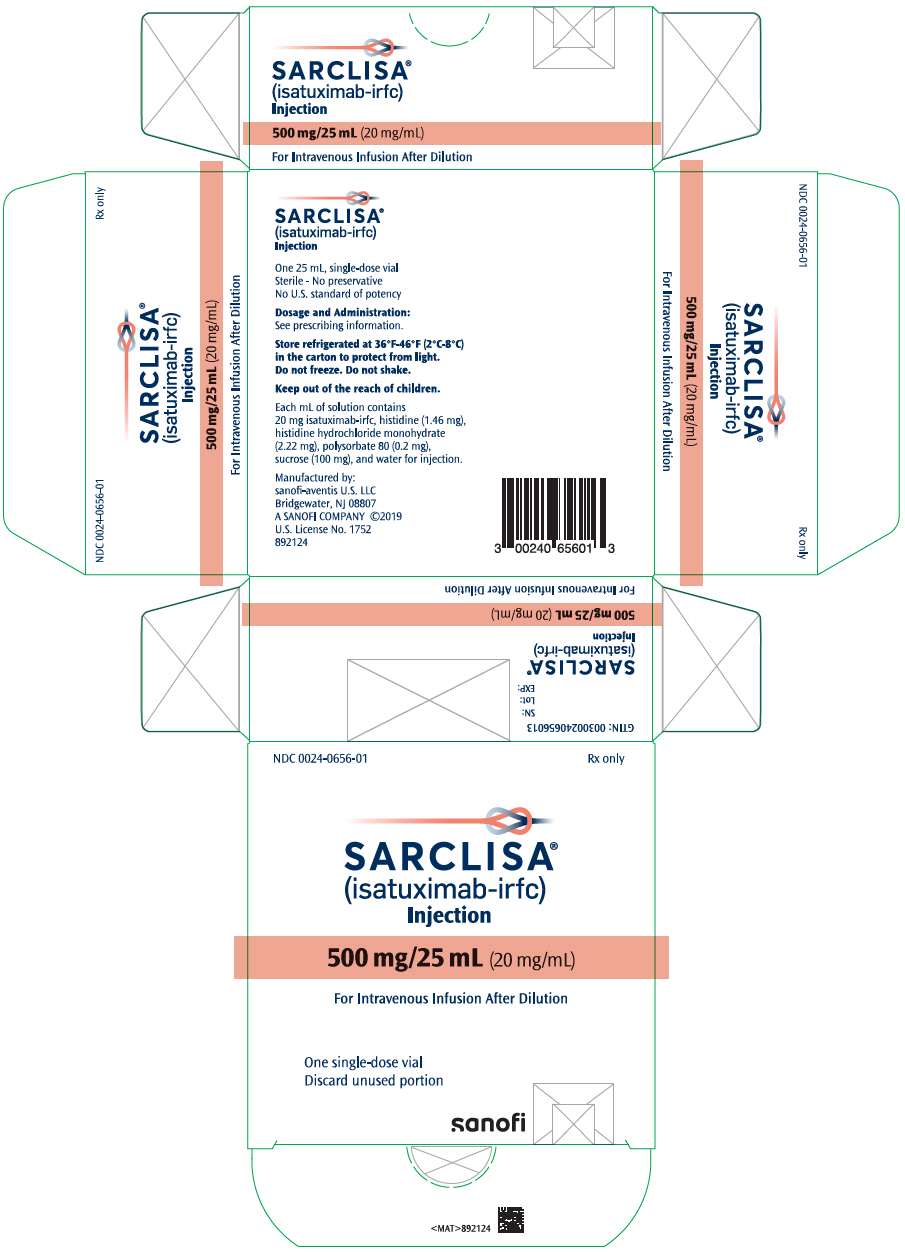 DRUG LABEL: Sarclisa
NDC: 0024-0654 | Form: INJECTION, SOLUTION, CONCENTRATE
Manufacturer: Sanofi-Aventis U.S. LLC
Category: prescription | Type: HUMAN PRESCRIPTION DRUG LABEL
Date: 20250616

ACTIVE INGREDIENTS: ISATUXIMAB 100 mg/5 mL
INACTIVE INGREDIENTS: SUCROSE 500 mg/5 mL; HISTIDINE MONOHYDROCHLORIDE MONOHYDRATE 11.1 mg/5 mL; HISTIDINE 7.3 mg/5 mL; POLYSORBATE 80 1 mg/5 mL; WATER

HIGHLIGHTS OF PRESCRIBING INFORMATION

These highlights do not include all the information needed to use SARCLISA safely and effectively. See full prescribing information for SARCLISA.
SARCLISA® (isatuximab-irfc) injection, for intravenous use
Initial U.S. Approval: 2020

RECENT MAJOR CHANGES

Indications and Usage (1) | 9/2024
Dosage and Administration (2.1, 2.2) | 9/2024
Warnings and Precautions (5.1, 5.2, 5.3, 5.4, 5.5) | 10/2024

1 INDICATIONS AND USAGE

SARCLISA is a CD38-directed cytolytic antibody indicated:

- in combination with pomalidomide and dexamethasone, for the treatment of adult patients with multiple myeloma who have received at least 2 prior therapies including lenalidomide and a proteasome inhibitor.
- in combination with carfilzomib and dexamethasone, for the treatment of adult patients with relapsed or refractory multiple myeloma who have received 1 to 3 prior lines of therapy.
- in combination with bortezomib, lenalidomide and dexamethasone, for the treatment of adult patients with newly diagnosed multiple myeloma who are not eligible for autologous stem cell transplant (ASCT). (1)

2 DOSAGE AND ADMINISTRATION

- Premedicate with dexamethasone, acetaminophen, H2 antagonists, and diphenhydramine. (2.2)
- The recommended dosage of SARCLISA is 10 mg/kg as an intravenous infusion. See full prescribing information for SARCLISA schedules of administration and drugs used in combination. (2.1)

3 DOSAGE FORMS AND STRENGTHS

Injection:

- 100 mg/5 mL (20 mg/mL) solution in single-dose vial (3)
- 500 mg/25 mL (20 mg/mL) solution in single-dose vial (3)

4 CONTRAINDICATIONS

Patients with severe hypersensitivity to isatuximab-irfc or to any of its excipients. (4)

5 WARNINGS AND PRECAUTIONS

- Infusion-Related Reactions: In case of grade ≥2, interrupt SARCLISA and manage medically. Permanently discontinue for grade 4 infusion-related reactions or anaphylactic reaction. (5.1)
- Infections: SARCLISA can cause serious and fatal infections. Monitor patients for signs and symptoms of infection and treat appropriately. (5.2)
- Neutropenia: Monitor complete blood cell counts periodically during treatment. Monitor patients with neutropenia for signs of infection. SARCLISA dose delays and the use of colony-stimulating factor may be required to allow improvement of neutrophil count. (5.3)
- Second Primary Malignancies (SPM): Monitor patients for the development of second primary malignancies. (5.4)
- Laboratory Test Interference:
  - Interference with Serological Testing (Indirect Antiglobulin Test): Type and screen patients prior to starting treatment. Inform blood banks that a patient has received SARCLISA. (5.5, 7.1)
  - Interference with Serum Protein Electrophoresis and Immunofixation Tests: SARCLISA may interfere with the assays used to monitor M-protein, which may impact the determination of complete response. (5.5, 7.1)
- Embryo-Fetal Toxicity: Can cause fetal harm. (5.6)

6 ADVERSE REACTIONS

- In combination with pomalidomide and dexamethasone: The most common adverse reactions (≥20%) are upper respiratory tract infection, infusion-related reactions, pneumonia, and diarrhea. The most common hematology laboratory abnormalities (≥80%) are decreased hemoglobin, decreased neutrophils, decreased lymphocytes, and decreased platelets. (6.1)
- In combination with carfilzomib and dexamethasone: The most common adverse reactions (≥20%) are upper respiratory tract infection, infusion-related reactions, fatigue, hypertension, diarrhea, pneumonia, dyspnea, insomnia, bronchitis, cough, and back pain. The most common hematology laboratory abnormalities (≥80%) are decreased hemoglobin, decreased lymphocytes, and decreased platelets. (6.1)
- In combination with bortezomib, lenalidomide and dexamethasone: The most common adverse reactions (≥20%) are upper respiratory tract infections, diarrhea, fatigue, peripheral sensory neuropathy, pneumonia, musculoskeletal pain, cataract, constipation, peripheral edema, rash, infusion-related reaction, insomnia, and COVID-19. The most common hematologic laboratory abnormalities (≥80%) are decreased hemoglobin, decreased leukocytes, decreased lymphocytes, decreased platelets, and decreased neutrophils. (6.1)

To report SUSPECTED ADVERSE REACTIONS, contact sanofi-aventis U.S. LLC at 1-800-633-1610 or FDA at 1-800-FDA-1088 or www.fda.gov/medwatch.

8 USE IN SPECIFIC POPULATIONS

Lactation: Advise not to breastfeed. (8.2)

FULL PRESCRIBING INFORMATION

1 INDICATIONS AND USAGE

SARCLISA is indicated:

- in combination with pomalidomide and dexamethasone, for the treatment of adult patients with multiple myeloma who have received at least 2 prior therapies including lenalidomide and a proteasome inhibitor.
- in combination with carfilzomib and dexamethasone, for the treatment of adult patients with relapsed or refractory multiple myeloma who have received 1 to 3 prior lines of therapy.
- in combination with bortezomib, lenalidomide, and dexamethasone, for the treatment of adult patients with newly diagnosed multiple myeloma who are not eligible for autologous stem cell transplant (ASCT).

2 DOSAGE AND ADMINISTRATION

2.1 Recommended Dosage

- Administer pre-infusion medications [see Dosage and Administration (2.2)].
- SARCLISA should be administered by a healthcare professional, with immediate access to emergency equipment and appropriate medical support to manage infusion-related reactions if they occur [see Warnings and Precautions (5.1)].

The recommended dose of SARCLISA is 10 mg/kg actual body weight administered as an intravenous infusion in combination with pomalidomide and dexamethasone or in combination with carfilzomib and dexamethasone, or in combination with bortezomib, lenalidomide, and dexamethasone.

SARCLISA dosing schedules are provided in Tables 1 and 2 [see Clinical Studies (14)].

Table 1: SARCLISA Dosing Schedule in Combination with Pomalidomide and Dexamethasone or in Combination with Carfilzomib and Dexamethasone
Cycles | Dosing schedules
Cycle 1 (28-day cycle) | Days 1, 8, 15, and 22 (weekly)
Cycle 2 and beyond (28-day cycles) | Days 1, 15 (every 2 weeks)

Table 2: SARCLISA Dosing Schedule in Combination with Bortezomib, Lenalidomide, and Dexamethasone
Cycles | Dosing schedules
Cycle 1 (42-day cycle) | Days 1, 8, 15, 22, and 29
Cycles 2 to 4 (42-day cycles) | Days 1, 15, and 29 (every 2 weeks)
Cycles 5 to 17 (28-day cycles) | Days 1 and 15 (every 2 weeks)
Cycles 18 and beyond (28-day cycles) | Day 1 (every 4 weeks)

Treatment is repeated until disease progression or unacceptable toxicity.

SARCLISA is used in combination with pomalidomide and dexamethasone or in combination with carfilzomib and dexamethasone or in combination with bortezomib, lenalidomide, and dexamethasone. For dosing instructions of combination agents administered with SARCLISA, see Clinical Studies (14) and manufacturer's prescribing information.

Missed SARCLISA Doses

If a planned dose of SARCLISA is missed, administer the dose as soon as possible and adjust the treatment schedule accordingly, maintaining the treatment interval.

2.2 Recommended Premedications and Antimicrobial Prophylaxis

Recommended Premedications

Administer the following premedications prior to SARCLISA infusion to reduce the risk and severity of infusion-related reactions [see Warnings and Precautions (5.1)]:

- When administered in combination with SARCLISA and pomalidomide: Dexamethasone 40 mg orally or intravenously (or 20 mg orally or intravenously for patients ≥75 years of age).
  When administered in combination with SARCLISA and carfilzomib: Dexamethasone 20 mg (intravenously on the days of SARCLISA and/or carfilzomib infusions, orally on day 22 in cycle 2 and beyond, and orally on day 23 in all cycles).
  When administered in combination with SARCLISA, bortezomib, and lenalidomide: Dexamethasone 20 mg (intravenously on the days of SARCLISA infusions, orally on the other days).
- Acetaminophen 650 mg to 1,000 mg orally (or equivalent).
- H2 antagonist
- Diphenhydramine 25 mg to 50 mg orally or intravenously (or equivalent). The intravenous route is preferred for at least the first 4 infusions.

The above recommended dose of dexamethasone (orally or intravenously) corresponds to the dose to be administered before infusion as part of the premedication and part of the backbone treatment. Administer dexamethasone before SARCLISA and pomalidomide, before SARCLISA and carfilzomib, and before SARCLISA, bortezomib, and lenalidomide administration.

Administer the recommended premedication agents 15 to 60 minutes prior to starting a SARCLISA infusion.

Recommended Antimicrobial Prophylaxis

Initiate antibacterial and antiviral prophylaxis (such as herpes zoster prophylaxis) if needed based on standard guidelines [see Warnings and Precautions (5.2)].

2.3 Dosage Modifications

No dose reduction of SARCLISA is recommended. Dose delay may be required to allow recovery of blood counts in the event of hematological toxicity [see Warnings and Precautions (5.3, 5.5)]. For information concerning drugs given in combination with SARCLISA, see manufacturer's prescribing information.

2.4 Preparation

Prepare the solution for infusion using aseptic technique as follows:

Calculate the dose (mg) of required SARCLISA based on actual patient weight (measured prior to each cycle to have the administered dose adjusted accordingly) [see Dosage and Administration (2.1)]. More than one SARCLISA vial may be necessary to obtain the required dose for the patient.

- Parenteral drug products should be inspected visually for particulate matter and discoloration prior to administration, whenever solution and container permit.
- Remove the volume of diluent from the 250 mL Sodium Chloride Injection, or 5% Dextrose Injection, diluent bag that is equal to the required volume of SARCLISA injection.
- Withdraw the necessary volume of SARCLISA injection from the vial and dilute by adding to the infusion bag of 0.9% Sodium Chloride Injection, or 5% Dextrose Injection. Discard any unused portion left in the vial.
- The infusion bag must be made of polyolefins (PO), polyethylene (PE), polypropylene (PP), polyvinyl chloride (PVC) with di-(2-ethylhexyl) phthalate (DEHP) or ethyl vinyl acetate (EVA).
- Gently homogenize the diluted solution by inverting the bag. Do not shake.

2.5 Administration

- Administer the infusion solution by intravenous infusion using an intravenous tubing infusion set (in PE, PVC with or without DEHP, polybutadiene [PBD], or polyurethane [PU]) with a 0.22 micron in-line filter (polyethersulfone [PES], polysulfone, or nylon).
- The infusion solution should be administered for a period of time that will depend on the infusion rate (see Table 3). Use prepared SARCLISA infusion solution within 48 hours when stored refrigerated at 2°C to 8°C, followed by 8 hours (including the infusion time) at room temperature.
- Do not administer SARCLISA infusion solution concomitantly in the same intravenous line with other agents.
- On the days where both SARCLISA and carfilzomib are administered, administer dexamethasone first, followed by SARCLISA infusion, then followed by carfilzomib infusion.

Infusion Rates

Following dilution, administer the SARCLISA infusion solution intravenously at the infusion rates presented in Table 3. Incremental escalation of the infusion rate should be considered only in the absence of infusion-related reactions [see Warnings and Precautions (5.1) and Adverse Reactions (6.1)].

Table 3: Infusion Rates of SARCLISA Administration
 | Dilution Volume | Initial Rate | Absence of Infusion-Related Reaction | Rate Increment | Maximum Rate
First infusion | 250 mL | 25 mL/hour | For 60 minutes | 25 mL/hour every 30 minutes | 150 mL/hour
Second infusion | 250 mL | 50 mL/hour | For 30 minutes | 50 mL/hour for 30 minutes then increase by 100 mL/hour | 200 mL/hour
Subsequent infusions | 250 mL | 200 mL/hour | – | – | 200 mL/hour

3 DOSAGE FORMS AND STRENGTHS

SARCLISA is a clear to slightly opalescent, colorless to slightly yellow solution, essentially free of visible particulates available as:

- Injection: 100 mg/5 mL (20 mg/mL) in a single-dose vial
- Injection: 500 mg/25 mL (20 mg/mL) in a single-dose vial

4 CONTRAINDICATIONS

SARCLISA is contraindicated in patients with severe hypersensitivity to isatuximab-irfc or to any of its excipients [see Warnings and Precautions (5.1)].

5 WARNINGS AND PRECAUTIONS

5.1 Infusion-Related Reactions

Serious infusion-related reactions including life-threatening anaphylactic reactions have occurred with SARCLISA treatment. Severe signs and symptoms included cardiac arrest, hypertension, hypotension, bronchospasm, dyspnea, angioedema, and swelling. In clinical trials (ICARIA-MM, IKEMA, and IMROZ), in patients treated with SARCLISA (N=592), infusion-related reactions occurred in 206 patients (35%). Among these 206 patients, 92% experienced infusion-related reactions during the first infusion and 12% after the first cycle. The most common symptoms (≥5%) of an infusion-related reaction included dyspnea and cough. Grade 1 infusion-related reactions were reported in 6% of patients, grade 2 in 28%, and grade 3 or 4 in 1.2%. Anaphylactic reactions occurred in less than 1% of patients. The total incidence of SARCLISA infusion interruptions was less than 1% and the incidence of patients with at least one SARCLISA infusion interruption due to infusion-related reactions was 26%. The median time to first SARCLISA infusion interruption was 61 minutes (range 4 to 240 minutes). SARCLISA was discontinued in 1% of patients due to infusion-related reactions.

To decrease the risk and severity of infusion-related reactions, premedicate patients prior to SARCLISA infusion with acetaminophen, H2 antagonists, diphenhydramine, or equivalent, and dexamethasone [see Dosage and Administration (2.2)].

Monitor vital signs frequently during the entire SARCLISA infusion. For patients with grade ≥2 reactions, interrupt SARCLISA infusion and provide appropriate medical management. For patients with grade 2 or grade 3 reactions, if symptoms improve to grade ≤1, restart SARCLISA infusion at half of the initial infusion rate, with supportive care as needed, and closely monitor patients. If symptoms do not recur after 30 minutes, the infusion rate may be increased to the initial rate, and then increased incrementally, as shown in Table 3 [see Dosage and Administration (2.5)]. In case symptoms do not improve to grade ≤1 after interruption of SARCLISA infusion, persist or worsen despite appropriate medications, or require hospitalization, permanently discontinue SARCLISA and institute appropriate management. Permanently discontinue SARCLISA if an anaphylactic reaction or life-threatening (grade 4) infusion-related reaction occurs and institute appropriate management.

5.2 Infections

SARCLISA can cause severe, life-threatening, or fatal infections. In patients who received SARCLISA at the recommended dose in ICARIA-MM, IKEMA, and IMROZ (N=592), serious infections, including opportunistic infections, occurred in 46% of patients, grade 3 or 4 infections occurred in 43%, and fatal infections occurred in 4.7%. The most common type of serious infection reported was pneumonia (32%).

Monitor patients for signs and symptoms of infection prior to and during treatment with SARCLISA and treat appropriately. Administer prophylactic antimicrobials according to guidelines [see Dosage and Administration (2.2)].

5.3 Neutropenia

SARCLISA can cause neutropenia.

In clinical trials (ICARIA-MM, IKEMA, and IMROZ), in patients treated with SARCLISA (N=592), neutropenia based on laboratory values occurred in 81%, with grade 3 or 4 occurring in 52%. Neutropenic infections occurred in 12% of patients, with grade 3 or 4 in 4.9%, and febrile neutropenia in 4% [see Adverse Reactions (6.1)].

Monitor complete blood cell counts periodically during treatment. If needed, use antibacterial and antiviral prophylaxis during treatment [see Dosage and Administration (2.2)]. Monitor patients with neutropenia for signs of infection. In case of grade 4 neutropenia delay SARCLISA dose until neutrophil count recovery to at least 1 × 10^9/L, and provide supportive care with growth factors, according to institutional guidelines. No dose reductions of SARCLISA are recommended.

5.4 Second Primary Malignancies

The incidence of second primary malignancies, during treatment and post-treatment, is increased in patients treated with SARCLISA-containing regimens. In clinical trials (ICARIA-MM, IKEMA, and IMROZ), in patients treated with SARCLISA (N=592), second primary malignancies occurred in 71 patients (12%).

In ICARIA-MM, at a median follow-up time of 52 months, second primary malignancies occurred in 7% of patients in the Isa-Pd arm and in 2% of patients in the Pd arm.

In IKEMA study, at a median follow-up time of 57 months, second primary malignancies occurred in 10% of patients in the Isa-Kd arm and in 8% of patients in the Kd arm.

In IMROZ study, at a median follow-up time of 60 months, second primary malignancies occurred in 16% of patients in the Isa-VRd arm and in 9% of patients in the VRd arm.

The most common (≥1%) second primary malignancies in ICARIA-MM, IKEMA, and IMROZ (N=592) included skin cancers (7% with SARCLISA-containing regimens and 3.1% with comparative regimens) and solid tumors other than skin cancer (4.6% with SARCLISA-containing regimens and 2.9% with comparative regimens). Patients with non-melanoma skin cancer continued treatment after resection of the skin cancer, except 2 patients on the Isa-VRd arm and 1 patient on the VRd arm of the IMROZ study.

Monitor patients for the development of second primary malignancies.

5.5 Laboratory Test Interference

Interference with Serological Testing (Indirect Antiglobulin Test)

SARCLISA binds to CD38 on red blood cells (RBCs) and may result in a false positive indirect antiglobulin test (indirect Coombs test). This interference with the indirect Coombs test may persist for approximately 6 months after the last infusion of SARCLISA. The indirect antiglobulin test was positive during Isa-Pd treatment in 68% of the tested patients, and during Isa-Kd treatment in 63% of patients. In patients with a positive indirect antiglobulin test, blood transfusions were administered without evidence of hemolysis. ABO/RhD typing was not affected by SARCLISA treatment.

Before the first SARCLISA infusion, conduct blood type and screen tests on SARCLISA-treated patients. Consider phenotyping prior to starting SARCLISA treatment. If treatment with SARCLISA has already started, inform the blood bank that the patient is receiving SARCLISA and SARCLISA interference with blood compatibility testing can be resolved using dithiothreitol-treated RBCs. If an emergency transfusion is required, non–cross-matched ABO/RhD-compatible RBCs can be given as per local blood bank practices [see Drug Interactions (7.1)].

Interference with Serum Protein Electrophoresis and Immunofixation Tests

SARCLISA is an IgG kappa monoclonal antibody that can be incidentally detected on both serum protein electrophoresis and immunofixation assays used for the clinical monitoring of endogenous M-protein. This interference can impact the accuracy of the determination of complete response in some patients with IgG kappa myeloma protein [see Drug Interactions (7.1)].

5.6 Embryo-Fetal Toxicity

Based on the mechanism of action, SARCLISA can cause fetal harm when administered to a pregnant woman. SARCLISA may cause fetal immune cell depletion and decreased bone density. Advise pregnant women of the potential risk to a fetus. Advise females with reproductive potential to use an effective method of contraception during treatment with SARCLISA and for 5 months after the last dose [see Use in Specific Populations (8.1, 8.3)]. The combination of SARCLISA with pomalidomide or lenalidomide is contraindicated in pregnant women because pomalidomide or lenalidomide may cause birth defects and death of the unborn child. Refer to the pomalidomide or lenalidomide prescribing information on use during pregnancy.

6 ADVERSE REACTIONS

The following clinically significant adverse reactions from SARCLISA are also described in other sections of the labeling:

- Infusion-Related Reactions [see Warnings and Precautions (5.1)]
- Infections [see Warnings and Precautions (5.2)]
- Neutropenia [see Warnings and Precautions (5.3)]
- Second Primary Malignancies [see Warnings and Precautions (5.4)]

6.1 Clinical Trials Experience

Because clinical trials are conducted under widely varying conditions, adverse reaction rates observed in the clinical trials of a drug cannot be directly compared to rates in the clinical trials of another drug and may not reflect the rates observed in practice.

Relapsed and/or Refractory Multiple Myeloma

Combination treatment with pomalidomide and dexamethasone (Isa-Pd)

The safety of SARCLISA was evaluated in ICARIA-MM, a randomized, open-label clinical trial in patients with previously treated multiple myeloma. Patients received SARCLISA 10 mg/kg intravenously, weekly in the first cycle and every two weeks thereafter, in combination with pomalidomide and dexamethasone (Isa-Pd) (n=152) or pomalidomide and dexamethasone (Pd) (n=149) [see Clinical Studies (14)]. Among patients receiving Isa-Pd, 66% were exposed to SARCLISA for 6 months or longer and 24% were exposed for greater than 12 months or longer.

Serious adverse reactions occurred in 62% of patients receiving Isa-Pd. Serious adverse reactions in >5% of patients who received Isa-Pd included pneumonia (26%), upper respiratory tract infections (7%), and febrile neutropenia (7%). Fatal adverse reactions occurred in 11% of patients (those that occurred in more than 1% of patients were pneumonia and other infections [3%]).

Permanent treatment discontinuation due to an adverse reaction (grades 1–4) occurred in 7% of patients who received Isa-Pd. The most frequent adverse reactions requiring permanent discontinuation in patients who received Isa-Pd were infections (2.6%). SARCLISA alone was discontinued in 3% of patients due to infusion-related reactions.

Dosage interruptions due to an adverse reaction occurred in 31% of patients who received SARCLISA. The most frequent adverse reaction requiring dosage interruption was infusion-related reaction (28%).

The most common adverse reactions (≥20%) were upper respiratory tract infection, infusion-related reactions, pneumonia, and diarrhea.

Table 4 summarizes the adverse reactions in ICARIA-MM.

Table 4: Adverse Reactions (≥10%) in Patients Receiving SARCLISA, Pomalidomide, and Dexamethasone with a Difference Between Arms of ≥5% Compared to Control Arm in ICARIA-MM Trial
Adverse Reactions | SARCLISA + Pomalidomide + Dexamethasone (Isa-Pd) |  |  | Pomalidomide + Dexamethasone (Pd)
 | (N=152) |  |  | (N=149)
 | All Grades (%) | Grade 3 (%) | Grade 4 (%) | All Grades (%) | Grade 3 (%) | Grade 4 (%)
General disorders and administration site conditions
Infusion-related reaction [Infusion-related reaction includes infusion-related reaction, cytokine release syndrome, and drug hypersensitivity.] | 38 | 1.3 | 1.3 | 0 | 0 | 0
Infections
Upper respiratory tract infection [Upper respiratory tract infection includes bronchiolitis, bronchitis, bronchitis viral, chronic sinusitis, fungal pharyngitis, influenza-like illness, laryngitis, nasopharyngitis, parainfluenzae virus infection, pharyngitis, respiratory tract infection, respiratory tract infection viral, rhinitis, sinusitis, tracheitis, upper respiratory tract infection, and upper respiratory tract infection bacterial.] | 57 | 9 | 0 | 42 | 3.4 | 0
Pneumonia [Pneumonia includes atypical pneumonia, bronchopulmonary aspergillosis, pneumonia, pneumonia haemophilus, pneumonia influenzal, pneumonia pneumococcal, pneumonia streptococcal, pneumonia viral, candida pneumonia, pneumonia bacterial, haemophilus infection, lung infection, pneumonia fungal, and pneumocystis jirovecii pneumonia.] | 31 | 22 | 3.3 | 23 | 16 | 2.7
Blood and lymphatic system disorders
Febrile neutropenia | 12 | 11 | 1.3 | 2 | 1.3 | 0.7
Respiratory, thoracic and mediastinal disorders
Dyspnea [Dyspnea includes dyspnea, dyspnea exertional, and dyspnea at rest.] | 17 | 5 | 0 | 12 | 1.3 | 0
Gastrointestinal disorders
Diarrhea | 26 | 2 | 0 | 19 | 0.7 | 0
Nausea | 15 | 0 | 0 | 9 | 0 | 0
Vomiting | 12 | 1.3 | 0 | 3.4 | 0 | 0
CTCAE version 4.03

Table 5 summarizes the hematology laboratory abnormalities in ICARIA-MM.

Table 5: Hematology Laboratory Abnormalities During the Treatment Period in Patients Receiving Isa-Pd versus Pd in ICARIA-MM
Laboratory Parameter | SARCLISA + Pomalidomide + Dexamethasone (Isa-Pd) |  |  | Pomalidomide + Dexamethasone (Pd)
 | (N=152) |  |  | (N=149)
 | All Grades (%) | Grade 3 (%) | Grade 4 (%) | All Grades (%) | Grade 3 (%) | Grade 4 (%)
Hemoglobin decreased | 99 | 32 | 0 | 97 | 28 | 0
Neutrophils decreased | 96 | 24 | 61 | 92 | 38 | 31
Lymphocytes decreased | 92 | 42 | 13 | 92 | 35 | 8
Platelets decreased | 84 | 14 | 16 | 79 | 9 | 15
The denominator used to calculate the percentages was based on the safety population.

Combination treatment with carfilzomib and dexamethasone (Isa-Kd)

The safety of SARCLISA was evaluated in IKEMA, a randomized, open-label clinical trial in patients with previously treated multiple myeloma. Patients received SARCLISA 10 mg/kg intravenously weekly in the first cycle, and every two weeks thereafter, in combination with carfilzomib and dexamethasone (Isa-Kd) (n=177) or carfilzomib and dexamethasone (Kd) (n=122) [see Clinical Studies (14)]. Among patients receiving Isa-Kd, 68% were exposed to SARCLISA for 12 months or longer and 51% were exposed for greater than 18 months.

Serious adverse reactions occurred in 59% of patients receiving Isa-Kd. The most frequent serious adverse reactions in >5% of patients who received Isa-Kd were pneumonia (25%) and upper respiratory tract infections (9%). Adverse reactions with a fatal outcome during treatment were reported in 3.4% of patients in the Isa-Kd group (those occurring in more than 1% of patients were pneumonia occurring in 1.7% and cardiac failure in 1.1% of patients).

Permanent treatment discontinuation due to an adverse reaction (grades 1–4) occurred in 8% of patients who received Isa-Kd. The most frequent adverse reactions requiring permanent discontinuation in patients who received Isa-Kd were infections (2.8%). SARCLISA alone was discontinued in 0.6% of patients due to infusion-related reactions.

Dosage interruptions due to an adverse reaction occurred in 33% of patients who received SARCLISA. The most frequent adverse reaction requiring dosage interruption was infusion-related reaction (30%).

The most common adverse reactions (≥20%) were upper respiratory tract infection, infusion-related reactions, fatigue, hypertension, diarrhea, pneumonia, dyspnea, insomnia, bronchitis, cough, and back pain.

Table 6 summarizes the adverse reactions in IKEMA.

Table 6: Adverse Reactions (≥10%) in Patients Receiving SARCLISA, Carfilzomib, and Dexamethasone with a Difference Between Arms of ≥5% Compared to Control Arm in IKEMA
Adverse Reactions | SARCLISA + Carfilzomib + Dexamethasone (Isa-Kd) |  |  | Carfilzomib + Dexamethasone (Kd)
 | (N=177) |  |  | (N=122)
 | All Grades (%) | Grade 3 (%) | Grade 4 (%) | All Grades (%) | Grade 3 (%) | Grade 4 (%)
General disorders and administration site conditions
Infusion-related reaction [Infusion-related reaction includes infusion-related reaction, cytokine release syndrome, and hypersensitivity.] | 46 | 0.6 | 0 | 3.3 | 0 | 0
Fatigue [Fatigue includes fatigue and asthenia.] | 42 | 5 | 0 | 32 | 3.3 | 0
Infections
Upper respiratory tract infection [Upper respiratory tract infection includes acute sinusitis, chronic sinusitis, H1N1 influenza, H3N2 influenza, influenza, laryngitis, laryngitis viral, nasal herpes, nasopharyngitis, pharyngitis, pharyngotonsillitis, respiratory syncytial virus infection, rhinitis, sinusitis, sinusitis bacterial, tonsillitis, tracheitis, upper respiratory tract infection, viral rhinitis, respiratory tract infection, respiratory tract infection viral, influenza like illness, parainfluenzae virus infection, respiratory tract infection bacterial, and viral upper respiratory tract infection.] | 67 | 9 | 0 | 57 | 7 | 0
Pneumonia [Pneumonia includes atypical pneumonia, lower respiratory tract infection, lower respiratory tract infection viral, pneumocystis jirovecii pneumonia, pneumonia, pneumonia influenzal, pneumonia legionella, pneumonia pneumococcal, pneumonia respiratory syncytial viral, pneumonia streptococcal, pneumonia viral, pulmonary sepsis, and pulmonary tuberculosis.] | 36 | 19 | 3.4 | 30 | 15 | 2.5
Bronchitis [Bronchitis includes bronchitis, bronchitis viral, respiratory syncytial virus bronchitis, bronchitis chronic, and tracheobronchitis.] | 24 | 2.3 | 0 | 13 | 0.8 | 0
Vascular disorders
Hypertension [Hypertension includes hypertension, blood pressure increased, and hypertensive crisis.] | 37 | 20 | 0.6 | 32 | 18 | 1.6
Respiratory, thoracic and mediastinal disorders
Dyspnea [Dyspnea includes dyspnea and dyspnea exertional.] | 29 | 5 | 0 | 24 | 0.8 | 0
Cough [Cough includes cough, productive cough, and allergic cough.] | 23 | 0 | 0 | 15 | 0 | 0
Gastrointestinal disorders
Diarrhea | 36 | 2.8 | 0 | 29 | 2.5 | 0
Vomiting | 15 | 1.1 | 0 | 9 | 0.8 | 0

Table 7 summarizes the hematology laboratory abnormalities in IKEMA.

Table 7: Hematology Laboratory Abnormalities During the Treatment Period in Patients Receiving Isa-Kd versus Kd in IKEMA
Laboratory Parameter | SARCLISA + Carfilzomib + Dexamethasone (Isa-Kd) |  |  | Carfilzomib + Dexamethasone (Kd)
 | (N=177) |  |  | (N=122)
 | All Grades (%) | Grade 3 (%) | Grade 4 (%) | All Grades (%) | Grade 3 (%) | Grade 4 (%)
Hemoglobin decreased | 99 | 22 | 0 | 99 | 20 | 0
Lymphocytes decreased | 94 | 52 | 17 | 95 | 43 | 14
Platelets decreased | 94 | 19 | 11 | 88 | 16 | 8
Neutrophils decreased | 55 | 18 | 1.7 | 43 | 7 | 0.8
The denominator used to calculate the percentage was based on the safety population.

Newly Diagnosed Multiple Myeloma not Eligible for Autologous Stem Cell Transplant

Combination treatment with bortezomib, lenalidomide, and dexamethasone (Isa-VRd)

The safety of SARCLISA was evaluated in IMROZ, a randomized, open-label clinical trial in patients with newly diagnosed multiple myeloma. Patients received SARCLISA 10 mg/kg intravenously on day 1, 8, 15, 22, and 29 in the first 42-day cycle, followed by every two weeks from cycle 2 to 4 (42-day cycles), followed by every two weeks from cycle 5 to 17 (28-day cycles), and then on day 1 from cycle 18 and onwards (28-day cycles), in combination with bortezomib, lenalidomide, and dexamethasone (Isa-VRd) (n=263) or bortezomib, lenalidomide, and dexamethasone (VRd) (n= 181) [see Clinical Studies (14)]. In IMROZ, median duration of exposure to treatment was 53 (range: 0.5–69) months in patients treated with Isa-VRd and 31 (range 0.6–67) months in patients treated with VRd.

Serious adverse reactions occurred in 71% of patients receiving Isa-VRd. The serious adverse reaction in > 5% of patients who received Isa-VRd was pneumonia (30%). Fatal adverse reactions occurred in 11% of patients with Isa-VRd (those occurring in more than 1% of patients were pneumonia (5%).

Permanent discontinuation of treatment due to an adverse reaction occurred in 22.8% of patients treated with Isa-VRd. The most frequent adverse reactions requiring permanent discontinuation in patients who received Isa-VRd were infections (8%). SARCLISA alone was discontinued in 2.3% of patients.

Dosage interruptions due to an adverse reaction occurred in 21% of patients who received SARCLISA. The most frequent adverse reaction requiring dosage interruption was infusion related reaction (21%).

The most common adverse reactions (≥20%) were upper respiratory tract infections, diarrhea, fatigue, peripheral sensory neuropathy, pneumonia, musculoskeletal pain, cataract, constipation, peripheral edema, rash, infusion-related reaction, insomnia, and COVID-19. The most common hematologic laboratory abnormalities (≥80%) were decreased hemoglobin, decreased leukocytes, decreased lymphocytes, decreased platelets, and decreased neutrophils.

Table 8 summarizes the adverse reactions in IMROZ.

Table 8: Adverse Reactions (≥ 20%) in Patients Receiving SARCLISA, Bortezomib, Lenalidomide, and Dexamethasone in IMROZ
 | IMROZ study
Adverse Reactions | SARCLISA + Bortezomib + Lenalidomide + Dexamethasone (N=263) |  | Bortezomib + Lenalidomide + Dexamethasone (N=181)
Adverse Reactions | All Grades (%) | Grade 3 or 4 (%) | All Grades (%) | Grade 3 or 4 (%)
Infections and infestations
Upper respiratory tract infection [Includes other related terms] | 65 | 4.6 | 57 [Includes 1 patient (0.6%) with fatal URTI.] | 6
Pneumonia [Pneumonia includes Atypical pneumonia, Bronchopulmonary aspergillosis, COVID-19 pneumonia, Lower respiratory tract infection, Pneumocystis jirovecii pneumonia, Pneumonia, Pneumonia aspiration, Pneumonia bacterial, Pneumonia influenzal, Pneumonia klebsiella, Pneumonia legionella, Pneumonia parainfluenzae viral, Pneumonia pneumococcal, Pneumonia pseudomonal, Pneumonia respiratory syncytial viral, Pneumonia viral, Pulmonary sepsis.] | 45 [Includes 14 patients (5%) with fatal pneumonia.] | 26 | 31 [Includes 4 patients (2.2%) with fatal pneumonia.] | 19
COVID-19 [COVID-19 includes COVID-19 infections other than COVID-19 pneumonia.] | 22 | 0.8 | 17 [Includes 2 patients (1.1%) with fatal COVID-19.] | 1.7
General disorders and administration site conditions
Fatigue [Fatigue includes Fatigue, Asthenia, or Malaise.] | 55 | 11 | 50 | 9
Edema peripheral | 33 | 0 | 33 | 1.1
Infusion-related reaction | 24 | 0.4 | 1.1 | 0
Gastrointestinal disorders
Diarrhea | 55 | 8 | 49 | 8
Constipation | 36 | 2.3 | 41 | 1.7
Nervous system disorders
Peripheral sensory neuropathy | 54 | 7 | 61 | 6
Eye disorders
Cataract | 38 | 16 | 25 | 11
Musculoskeletal and connective tissue disorders
Musculoskeletal pain | 38 | 4.2 | 33 | 3.3
Skin and subcutaneous tissue disorders
Rash [Rash includes Dermatitis, Dermatitis acneiform, Dermatitis allergic, Dermatitis atopic, Dermatitis exfoliative generalized, Drug eruption, Rash, Rash erythematous, Rash macular, Rash maculo-papular, Rash pruritic, Rash pustular, Skin exfoliation, Skin hyperpigmentation, Skin lesion, Skin reaction, and Toxic skin eruption.] | 32 | 5 | 34 | 5
Psychiatric disorders
Insomnia | 22 | 3.8 | 24 | 2.2

Table 9 summarizes the hematology laboratory abnormalities in IMROZ.

Table 9: Hematology Laboratory Abnormalities During the Treatment Period in Patients Receiving Isa-VRd Versus VRd in IMROZ
Laboratory parameter | SARCLISA + Bortezomib + Lenalidomide + Dexamethasone [The denominator used to calculate the rate is based on the number of patients with a baseline value and at least one post-baseline value.] |  | Bortezomib + Lenalidomide + Dexamethasone
Laboratory parameter | All Grades (%) | Grade 3–4 (%) | All Grades (%) | Grade 3–4 (%)
Decreased hemoglobin | 99 | 17 | 98 | 16
Decreased leukocytes | 97 | 32 | 88 | 17
Decreased lymphocytes | 95 | 60 | 92 | 53
Decreased platelets | 95 | 30 | 85 | 28
Decreased neutrophils | 87 | 54 | 80 | 37

Description of Selected Adverse Reactions

Cardiac failure

In IKEMA, cardiac failure (including cardiac failure, cardiac failure congestive, cardiac failure acute, cardiac failure chronic, left ventricular failure, and pulmonary edema) was reported in 7% of patients with the Isa-Kd group (grade ≥3 in 4%) and in 7% of patients with the Kd group (grade ≥3 in 4.1%). Serious cardiac failure was observed in 4% of patients in the Isa-Kd group and in 3.3% of patients in the Kd group. See the current prescribing information for carfilzomib for more information.

7 DRUG INTERACTIONS

7.1 Laboratory Test Interference

Interference with Serological Testing

SARCLISA, an anti-CD38 antibody, may interfere with blood bank serologic tests with false positive reactions in indirect antiglobulin tests (indirect Coombs tests), antibody detection (screening) tests, antibody identification panels, and antihuman globulin crossmatches in patients treated with SARCLISA [see Warnings and Precautions (5.5)].

Interference with Serum Protein Electrophoresis and Immunofixation Tests

SARCLISA may be incidentally detected by serum protein electrophoresis and immunofixation assays used for the monitoring of M-protein and may interfere with accurate response classification based on International Myeloma Working Group (IMWG) criteria [see Warnings and Precautions (5.5)]. In patients with persistent very good partial response, where interference is suspected, consider using an FDA-cleared isatuximab-irfc-specific IFE assay to distinguish isatuximab from any remaining endogenous M protein in the patient's serum to facilitate determination of a complete response.

8 USE IN SPECIFIC POPULATIONS

8.1 Pregnancy

Risk Summary

SARCLISA can cause fetal harm when administered to a pregnant woman. The assessment of isatuximab-irfc-associated risks is based on the mechanism of action and data from target antigen CD38 knockout animal models (see Data). There are no available data on SARCLISA use in pregnant women to evaluate for a drug-associated risk of major birth defects, miscarriage or adverse maternal or fetal outcomes. Animal reproduction toxicity studies have not been conducted with isatuximab-irfc. The estimated background risk of major birth defects and miscarriage for the indicated population is unknown. All pregnancies have a background risk of birth defect, miscarriage, or other adverse outcomes. In the U.S. general population, the estimated background risk of major birth defects and miscarriage in clinically recognized pregnancies is 2% to 4% and 15% to 20%, respectively.

The combination of SARCLISA and pomalidomide or lenalidomide is contraindicated in pregnant women because pomalidomide and lenalidomide may cause birth defects and death of the unborn child. Refer to the pomalidomide or lenalidomide prescribing information on use during pregnancy. Pomalidomide and lenalidomide are only available through a REMS program.

Clinical Considerations

Fetal/neonatal reactions

Immunoglobulin G1 monoclonal antibodies are known to cross the placenta. Based on its mechanism of action, SARCLISA may cause depletion of fetal CD38-positive immune cells and decreased bone density. Defer administration of live vaccines to neonates and infants exposed to SARCLISA in utero until a hematology evaluation is completed.

Data

Animal data

Mice that were genetically modified to eliminate all CD38 expression (CD38 knockout mice) had reduced bone density which recovered 5 months after birth. Data from studies using CD38 knockout animal models also suggest the involvement of CD38 in regulating humoral immune responses (mice), feto-maternal immune tolerance (mice), and early embryonic development (frogs).

8.2 Lactation

Risk Summary

There are no available data on the presence of isatuximab-irfc in human milk, milk production, or the effects on the breastfed child. Maternal immunoglobulin G is known to be present in human milk. The effects of local gastrointestinal exposure and limited systemic exposure in the breastfed infant to SARCLISA are unknown. Because of the potential for serious adverse reactions in the breastfed child from isatuximab-irfc administered in combination with pomalidomide or lenalidomide and dexamethasone, advise lactating women not to breastfeed during treatment with SARCLISA. Refer to pomalidomide or lenalidomide prescribing information for additional information.

8.3 Females and Males of Reproductive Potential

SARCLISA can cause fetal harm when administered to a pregnant woman [see Use in Specific Populations (8.1)].

Pregnancy Testing

With the combination of SARCLISA with pomalidomide or lenalidomide, refer to the pomalidomide or lenalidomide labeling for pregnancy testing requirements prior to initiating treatment in females of reproductive potential.

Contraception

Females

Advise female patients of reproductive potential to use effective contraception during treatment and for 5 months after the last dose of SARCLISA. Additionally, refer to the pomalidomide or lenalidomide labeling for contraception requirements prior to initiating treatment in females of reproductive potential.

Males

Refer to the pomalidomide or lenalidomide prescribing information.

8.4 Pediatric Use

The safety and effectiveness of SARCLISA in pediatric patients have not been established.

The safety and efficacy of SARCLISA in combination with chemotherapy were assessed, but not established, in an open-label study (ACT15378, ISAKIDS, NCT03860844) in 62 pediatric patients aged 1.4 years to < 17 years with relapsed or refractory T-acute lymphoblastic leukemia (T-ALL), B-acute lymphoblastic leukemia (B-ALL), or acute myeloid leukemia (AML). No new safety signals were observed in pediatric patients in this trial.

Body weight adjusted clearance at steady state and volume of distribution of isatuximab in pediatric patients were within the range of values that were observed in adults.

8.5 Geriatric Use

Of the total number of patients with relapsed or refractory multiple myeloma in clinical studies of SARCLISA, 56% (n=586) were 65 years of age and older, while 16% (n=163) were 75 years of age and older [see Clinical Studies (14)]. No overall differences in safety or effectiveness were observed between patients 65 years of age and older compared to younger patients, and other reported clinical experience has not identified differences in responses between the adults 65 years of age and older and younger patients, but greater sensitivity of some older individuals cannot be ruled out.

Of the total number of SARCLISA-treated patients with newly diagnosed multiple myeloma in IMROZ, 72% (n=319) were less than 75 years of age and 28% (n=125) were 75 years of age and older. The clinical trial did not enroll patients over age 80 [see Clinical Studies (14)]. Adverse reactions occurring at a higher frequency in the SARCLISA arm (≥5%) in patients 75 years of age and older included neutropenia. Adverse reactions leading to dose modifications in patients 75 years of age and older occurred at a higher frequency (≥5%) in the SARCLISA arm. The hazard ratio for overall survival (OS) in patients 75 years of age and older was 1.25 [95% CI: 0.68 to 2.3].

11 DESCRIPTION

Isatuximab-irfc, a CD38-directed cytolytic antibody, is a chimeric immunoglobulin G1 (IgG1) monoclonal antibody (mAb). Isatuximab-irfc is produced from a mammalian cell line (Chinese hamster ovary, CHO) using a fed-batch production process. Isatuximab-irfc is composed of two identical immunoglobulin kappa light chains and two identical immunoglobulin gamma heavy chains and has an overall molecular weight of approximately 148 kDa.

SARCLISA (isatuximab-irfc) injection is a sterile, preservative-free, clear to slightly opalescent, colorless to slightly yellow solution, essentially free of visible particles in a single-dose vial for intravenous use. Each vial contains either 100 mg/5 mL or 500 mg/25 mL of isatuximab-irfc at a concentration of 20 mg/mL with a pH of 6.0. Each mL of solution contains 20 mg isatuximab-irfc, histidine (1.46 mg), histidine hydrochloride monohydrate (2.22 mg), polysorbate 80 (0.2 mg), sucrose (100 mg), and water for injection.

12 CLINICAL PHARMACOLOGY

12.1 Mechanism of Action

Isatuximab-irfc is an IgG1-derived monoclonal antibody that binds to CD38 expressed on the surface of hematopoietic and tumor cells, including multiple myeloma cells. Isatuximab-irfc induces apoptosis of tumor cells and activation of immune effector mechanisms including antibody-dependent cell-mediated cytotoxicity (ADCC), antibody-dependent cellular phagocytosis (ADCP), and complement dependent cytotoxicity (CDC). Isatuximab-irfc inhibits the ADP-ribosyl cyclase activity of CD38. Isatuximab-irfc can activate natural killer (NK) cells in the absence of CD38-positive target tumor cells and suppresses CD38-positive T-regulatory cells. The combination of isatuximab-irfc and pomalidomide enhanced ADCC activity and direct tumor cell killing compared to that of isatuximab-irfc alone in vitro, and enhanced antitumor activity compared to the activity of isatuximab-irfc or pomalidomide alone in a human multiple myeloma xenograft model.

12.2 Pharmacodynamics

In multiple myeloma patients treated with SARCLISA combined with pomalidomide and dexamethasone, a decrease in absolute counts of total NK cells (including inflammatory CD16+ low CD56+ bright and cytotoxic CD16+ bright CD56+ dim NK cells) and CD19+ B cells was observed in peripheral blood.

Cardiac Electrophysiology

Up to 2 times the approved recommended dose, SARCLISA does not prolong the QT interval to any clinically relevant extent.

A relationship between isatuximab-irfc exposure and overall response rate and progression-free survival was observed.

No apparent relationship was observed between an increase of isatuximab-irfc exposure and adverse reactions.

12.3 Pharmacokinetics

Following administration of isatuximab-irfc in combination with pomalidomide and dexamethasone at the recommended dose and schedule, the steady-state mean (CV%) predicted maximum plasma concentration (Cmax) and area under the plasma concentration-time curve (AUC) of isatuximab-irfc were 351 µg/mL (36.0%) and 72,600 µg∙h/mL (51.7%), respectively.

Following administration of isatuximab-irfc in combination with carfilzomib and dexamethasone at the recommended dose and schedule, the steady state mean (CV%) predicted Cmax and AUC of isatuximab-irfc were 655 µg/mL (30.8%) and 159,000 µg∙h/mL (37.1%), respectively.

The median time to reach steady state of isatuximab-irfc was 18 weeks with a 3.1-fold accumulation.

Following administration of isatuximab-irfc in combination with bortezomib, lenalidomide, and dexamethasone at the recommended dose and schedule, the mean (CV%) predicted Cmax and AUC of isatuximab-irfc after the dose on Week 21 were 496 µg/mL (25.6%) and 120,000 µg∙h/mL (28.9%), respectively. The geometric mean (CV%) of accumulation ratio between steady state AUC and AUC after the dose on Week 21 is predicted to be 1.4 (35.8%). Isatuximab-irfc AUC increases in a greater than dose proportional manner over a dosage range from 1 mg/kg to 20 mg/kg (0.1 to 2 times the approved recommended dosage) every 2 weeks. Isatuximab-irfc AUC increases proportionally over a dosage range from 5 mg/kg to 20 mg/kg (0.5 to 2 times the approved recommended dosage) every week for 4 weeks followed by every 2 weeks.

Distribution

The mean (CV%) predicted total volume of distribution of isatuximab-irfc is of 8.13 L (26.2%).

Metabolism

Isatuximab-irfc is expected to be metabolized into small peptides by catabolic pathways.

Elimination

Isatuximab-irfc total clearance decreased with increasing dose and with multiple doses. At steady state, the near elimination (≥99%) of isatuximab-irfc from plasma after the last dose is predicted to occur in approximately 2 months. The elimination of isatuximab-irfc was similar when given as a single agent or as combination therapy.

Specific Populations

The following factors have no clinically meaningful effect on the exposure of isatuximab-irfc: age (36 to 85 years, 70 patients were ≥75 years old), sex, renal impairment including patients with End-Stage Renal Disease (ESRD) or on dialysis (eGFR <90 mL/min/1.73 m^2), and mild hepatic impairment (total bilirubin ≤ upper limit of normal [ULN] and aspartate aminotransferase [AST] >ULN, or total bilirubin >1 to 1.5 × ULN and any AST). The effect of moderate (total bilirubin >1.5 to 3 × ULN and any AST) and severe (total bilirubin >3 × ULN and any AST) hepatic impairment on isatuximab-irfc pharmacokinetics is unknown.

No dose adjustments are recommended in these specific patient populations.

Body weight

The clearance of isatuximab-irfc increased with increasing body weight.

Race

White (n=377, 79%) or Asian (n=25, 5%) race have no clinically meaningful effect on the exposure of isatuximab-irfc. The effect of Black (n=18, 4%) race on the exposure of isatuximab-irfc is unknown.

12.6 Immunogenicity

The observed incidence of anti-drug antibodies is highly dependent on the sensitivity and specificity of the assay. Differences in assay methods preclude meaningful comparisons of the incidence of anti-drug antibodies in the studies described below with the incidence of anti-drug antibodies in other studies, including those of isatuximab-irfc or of other isatuximab products.

Overall, across 9 clinical studies in relapsed and/or refractory multiple myeloma (RRMM) with SARCLISA single-agent and combination therapies including ICARIA-MM and IKEMA (N=1023), the incidence of treatment emergent anti-drug antibodies (ADAs) was <2%. In ICARIA-MM and IKEMA, no patients with RRMM tested positive for ADA. Therefore, the neutralizing ADA status was not determined. In RRMM, no effect of ADAs was observed on the pharmacokinetics, safety, or efficacy of SARCLISA.

In IMROZ, out of the 263 patients with NDMM treated with SARCLISA in combination with bortezomib, lenalidomide, and dexamethasone, 253 were evaluable for the presence of ADA, 22 patients (8.7%) tested positive for treatment-emergent ADAs, with 21 patients considered to have a transient ADA response and 1 considered to have an indeterminate ADA response. Among these 22 ADA-positive patients, 13 (5.9%) had neutralizing antibodies. In IMROZ, a trend to lower exposure was observed in ADA-positive patients, which was considered not clinically relevant. In patients with ADA-positive status to SARCLISA, including those with neutralizing antibodies, no meaningful impact of ADAs on safety or efficacy of SARCLISA was observed.

13 NONCLINICAL TOXICOLOGY

13.1 Carcinogenesis, Mutagenesis, Impairment of Fertility

Carcinogenicity and genotoxicity studies have not been conducted with isatuximab-irfc. Fertility studies have not been conducted with isatuximab-irfc.

14 CLINICAL STUDIES

Relapsed and/or Refractory Multiple Myeloma

ICARIA-MM

The efficacy and safety of SARCLISA in combination with pomalidomide and dexamethasone (Isa-Pd) were evaluated in ICARIA-MM (NCT02990338), a multicenter, multinational, randomized, open-label, 2-arm, phase 3 study in patients with relapsed and/or refractory multiple myeloma. Patients had received at least two prior therapies including lenalidomide and a proteasome inhibitor. Patients were eligible for inclusion if they had an Eastern Cooperative Oncology Group (ECOG) status of 0–2, platelets ≥75,000 cells/mm^3, absolute neutrophil count ≥1 × 10^9/L, creatinine clearance ≥30 mL/min/1.73 m^2 (MDRD formula), AST ≤3 × ULN, and ALT ≤3 × ULN.

A total of 307 patients were randomized in a 1:1 ratio to receive either SARCLISA in combination with pomalidomide and dexamethasone (Isa-Pd, 154 patients) or pomalidomide and dexamethasone (Pd, 153 patients). Treatment was administered in both groups in 28-day cycles until disease progression or unacceptable toxicity. SARCLISA 10 mg/kg was administered as an intravenous infusion weekly in the first cycle and every two weeks thereafter. Pomalidomide 4 mg was taken orally once daily from day 1 to day 21 of each 28-day cycle. Dexamethasone (orally or intravenously) 40 mg (20 mg for patients ≥75 years of age) was given on days 1, 8, 15, and 22 for each 28-day cycle.

Overall, demographic and disease characteristics at baseline were similar between the two treatment groups. The median patient age was 67 years (range 36–86), 20% of patients were ≥75 years; 79% of patients were White, 12% Asian, and 1% Black or African American; 10% of patients entered the study with a history of COPD or asthma. The proportion of patients with renal impairment (creatinine clearance <60 mL/min/1.73 m^2) was 34%. The International Staging System (ISS) stage at study entry was I in 37%, II in 36% and III in 25% of patients. Overall, 20% of patients had high-risk chromosomal abnormalities at study entry; del(17p), t(4;14) and t(14;16) were present in 12%, 8% and 2% of patients, respectively.

The median number of prior lines of therapy was 3 (range 2–11). All patients received a prior proteasome inhibitor, all patients received prior lenalidomide, and 56% of patients received prior stem cell transplantation; the majority of patients (93%) were refractory to lenalidomide, 76% to a proteasome inhibitor, and 73% to both an immunomodulator and a proteasome inhibitor.

The median duration of treatment was 41 weeks for Isa-Pd group compared to 24 weeks for Pd group.

The efficacy of SARCLISA was based upon progression-free survival (PFS). PFS results were assessed by an Independent Response Committee based on central laboratory data for M-protein and central radiologic imaging review using the International Myeloma Working Group (IMWG) criteria. The improvement in PFS represented a 40% reduction in the risk of disease progression or death in patients treated with Isa-Pd.

Efficacy results are presented in Table 10 and Kaplan-Meier curve for PFS is provided in Figure 1.

Table 10: Efficacy of SARCLISA in Combination with Pomalidomide and Dexamethasone versus Pomalidomide and Dexamethasone in the Treatment of Multiple Myeloma (ICARIA-MM)
Endpoint | SARCLISA + Pomalidomide + Dexamethasone N=154 | Pomalidomide + Dexamethasone N=153
Progression-Free Survival
Median (months) [95% CI] | 11.53 [8.94–13.9] | 6.47 [4.47–8.28]
Hazard ratio [Stratified-on age (<75 years versus ≥75 years) and number of previous lines of therapy (2 or 3 vs >3) according to IRT.] [95% CI] | 0.596 [0.44–0.81]
p-value (stratified log-rank test) | 0.0010
Overall Response Rate [sCR, CR, VGPR and PR were evaluated by the IRC using the IMWG response criteria.] Responders (sCR+CR+VGPR+PR) n (%) [95% CI] [Estimated using Clopper-Pearson method.] | 93 (60.4) [52.2–68.2] | 54 (35.3) [27.8–43.4]
p-value (stratified Cochran-Mantel-Haenszel) | <0.0001
Stringent Complete Response (sCR) + Complete Response (CR) n (%) | 7 (4.5) | 3 (2)
Very Good Partial Response (VGPR) n (%) | 42 (27.3) | 10 (6.5)
Partial Response (PR) n (%) | 44 (28.6) | 41 (26.8)

The median time to first response in responders was 35 days in the Isa-Pd group versus 58 days in the Pd group. The median duration of response was 13.3 months (95% CI: 10.6-NR) in the Isa-Pd group versus 11.1 months (95% CI: 8.5-NR) in the Pd group. At a median follow-up time of 52.4 months, final median overall survival was 24.6 months in the Isa-Pd group and 17.7 months in the Pd group (HR=0.776; 95% CI: 0.594 to 1.015).

Figure 1: Kaplan-Meier Curves of PFS – ITT Population – ICARIA-MM (assessment by the IRC)

IKEMA

The efficacy and safety of SARCLISA in combination with carfilzomib and dexamethasone were evaluated in IKEMA (NCT03275285), a multicenter, multinational, randomized, open-label, 2-arm, phase 3 study in patients with relapsed and/or refractory multiple myeloma. Patients had received one to three prior lines of therapy. Patients were eligible for inclusion if they had an ECOG status of 0–2, platelets ≥50,000 cells/mm^3, absolute neutrophil count ≥1 × 10^9/L, creatinine clearance ≥15 mL/min/1.73 m^2 (MDRD formula), AST ≤3 × ULN, and ALT ≤3 × ULN.

A total of 302 patients were randomized in a 3:2 ratio to receive either SARCLISA in combination with carfilzomib and dexamethasone (Isa-Kd, 179 patients) or carfilzomib and dexamethasone (Kd, 123 patients). Treatment was administered in both groups in 28-day cycles until disease progression or unacceptable toxicity. SARCLISA 10 mg/kg was administered as an intravenous infusion weekly in the first cycle and every two weeks thereafter. Carfilzomib was administered as an intravenous infusion at the dose of 20 mg/m^2 on days 1 and 2; 56 mg/m^2 on days 8, 9, 15, and 16 of cycle 1; and at the dose of 56 mg/m^2 on days 1, 2, 8, 9, 15, and 16 for subsequent cycles of each 28-day cycle. Dexamethasone (intravenously on the days of isatuximab-irfc and/or carfilzomib infusions, and orally on the other days) 20 mg was given on days 1, 2, 8, 9, 15, 16, 22, and 23 for each 28-day cycle. On the days where both SARCLISA and carfilzomib were administered, dexamethasone was administered first, followed by SARCLISA infusion, then followed by carfilzomib infusion.

Overall, demographic and disease characteristics at baseline were similar between the two treatment groups. The median patient age was 64 years (range 33–90), 9% of patients were ≥75 years, 71% were White, 17% Asian, and 3% Black or African American. The proportion of patients with renal impairment (eGFR<60 mL/min/1.73 m^2) was 24% in the Isa-Kd group versus 15% in the Kd group. The International Staging System (ISS) stage at study entry was I in 53%, II in 31%, and III in 15% of patients. Overall, 24% of patients had high-risk chromosomal abnormalities at study entry; del(17p), t(4;14), t(14;16) were present in 11%, 14%, and 2% of patients, respectively. In addition, gain(1q21) was present in 42% of patients.

The median number of prior lines of therapy was 2 (range 1–4) with 44% of patients who received 1 prior line of therapy. Overall, 90% of patients received prior proteasome inhibitors, 78% received prior immunomodulators (including 43% who received prior lenalidomide), and 61% received prior stem cell transplantation. Overall, 33% of patients were refractory to prior proteasome inhibitors, 45% were refractory to prior immunomodulators (including 33% refractory to lenalidomide), and 21% were refractory to both a proteasome inhibitor and an immunomodulator.

The median duration of treatment was 80 weeks for the Isa-Kd group compared to 61 weeks for the Kd group.

The efficacy of SARCLISA was based upon PFS. PFS results were assessed by an Independent Response Committee based on central laboratory data for M-protein and central radiologic imaging review using the IMWG criteria. The improvement in PFS represented a 45% reduction in the risk of disease progression or death in patients treated with Isa-Kd compared to patients treated with Kd.

Efficacy results are presented in Table 11 and Kaplan-Meier curves for PFS are provided in Figure 2.

Table 11 [Results are based on a prespecified interim analysis.] , [Median follow-up time 20.7 months.] : Efficacy of SARCLISA in Combination with Carfilzomib and Dexamethasone versus Carfilzomib and Dexamethasone in the Treatment of Multiple Myeloma (IKEMA)
Endpoint | SARCLISA + Carfilzomib + Dexamethasone N=179 | Carfilzomib + Dexamethasone N=123
Progression-Free Survival [PFS results were assessed by the IRC based on central laboratory data for M-protein and central radiologic imaging review using the IMWG criteria. A comparison is considered statistically significant if the p-value is <0.008 (efficacy boundary).]
Median (months) [95% CI] | NR [NR– NR] | 20.27 [15.77– NR]
Hazard ratio [Stratified on number of previous lines of therapy (1 versus >1) and R-ISS (I or II versus III versus not classified) according to IRT.] [95% CI] | 0.548 [0.366–0.822]
p-value (stratified log-rank test) | 0.0032
Overall Response Rate [sCR, CR, VGPR, and PR were evaluated by the IRC using the IMWG response criteria.] Responders (sCR+CR+VGPR+PR) n (%) [95% CI] [Estimated using Clopper-Pearson method.] | 155 (86.6) [80.7–91.2] | 102 (82.9) [75.1–89.1]
p-value (stratified Cochran-Mantel-Haenszel) | 0.3859
Complete Response (CR) n (%) | 71 (39.7) | 34 (27.6)
Very Good Partial Response (VGPR) n (%) | 59 (33) | 35 (28.5)
Partial Response (PR) n (%) | 25 (14) | 33 (26.8)
NR: not reached.

Figure 2: Kaplan-Meier Curves of PFS – ITT Population – IKEMA (assessment by the IRC)

At a median follow-up time of 44.0 months, final PFS analysis showed a median PFS of 41.7 months for Isa-Kd group compared to 20.8 months for Kd group, with a hazard ratio of 0.594 (95.4% CI: 0.424 to 0.832). Final complete response, determined using a FDA-cleared isatuximab-irfc-specific IFE assay [see Drug Interactions (7.1)], was 44.1% in Isa-Kd group compared to 28.5% in Kd group.

At a median follow-up time of 57 months, median overall survival was not reached in the Isa-Kd group (95% CI: 52.172–NR) and was 50.6 months in Kd group (95% CI: 38.932–NR) (HR=0.855; 95% CI: 0.608–1.202).

Newly Diagnosed Multiple Myeloma

IMROZ

The efficacy of SARCLISA in combination with bortezomib, lenalidomide, and dexamethasone was evaluated in IMROZ (NCT03319667), a multicenter, international, randomized, open-label, 2-arm, phase 3 study in patients with newly diagnosed multiple myeloma who are not eligible for stem cell transplantation. Patients were eligible for inclusion if they had an Eastern Cooperative Oncology Group (ECOG) status of 0 or 1, platelets ≥70,000 cells/mm^3, absolute neutrophil count ≥1 × 10^9/L, creatinine clearance ≥30 mL/min/1.73 m^2 (MDRD formula), AST ≤3 × ULN, and ALT ≤3 × ULN.

A total of 446 patients were randomized in a 3:2 ratio to receive either SARCLISA in combination with bortezomib, lenalidomide, and dexamethasone (Isa-VRd, 265 patients) or bortezomib, lenalidomide, and dexamethasone (VRd, 181 patients). Treatment was administered in both groups during 4 cycles of 42-days each for the induction period. After completion of cycle 4, patients entered the continuous treatment period starting from cycle 5, in which 28-day cycles were administered up to disease progression or unacceptable toxicity. During the continuous treatment period, patients of the Isa-VRd group received SARCLISA in combination with lenalidomide, and dexamethasone (Isa-Rd), and patients in the VRd group received lenalidomide, and dexamethasone (Rd). During the induction period (cycle 1 to 4, 42-day cycles), SARCLISA 10 mg/kg was administered as an intravenous infusion on day 1, 8, 15, 22, and 29, in the first cycle and on day 1, 15, and 29, from cycle 2 to 4. Bortezomib was administered subcutaneously at the dose of 1.3 mg/m^2 on days 1, 4, 8, 11, 22, 25, 29, and 32 of each cycle. Lenalidomide was administered orally at the dose of 25 mg/day from day 1 to 14 and from day 22 to 35 of each cycle. Dexamethasone (intravenously on the days of SARCLISA infusions, and orally on the other days) 20 mg/day was given on days 1, 2, 4, 5, 8, 9, 11, 12, 15, 22, 23, 25, 26, 29, 30, 32, and 33 of each cycle. During the continuous treatment period (from cycle 5, 28-day cycles), SARCLISA 10 mg/kg was administered as an IV infusion on day 1 and 15 from cycle 5 to 17, and on day 1 from cycle 18. Lenalidomide was administered orally at the dose of 25 mg/day from day 1 to 21 of each cycle. Dexamethasone (intravenously on the days of SARCLISA infusions, and orally on the other days) 20 mg/day was given on days 1, 8, 15, and 22 of each cycle.

The median patient age was 72 years (range 55–80), 28% of patients were ≥75 years; 72% of patients were White, 11% Asian, and 0.9% Black or African American. The proportion of patients with renal impairment (eGFR<60 mL/min/1.73m^2) was 29%. The Revised International Staging System (R-ISS) stage at study entry was I in 23%, II in 64%, and III in 10% of patients. Overall, 17% of patients had high-risk chromosomal abnormalities at study entry; del(17p), t(4;14), and t(14;16) were present in 5%, 9% and 2% of patients, respectively. In addition, 1q21+ was present in 37% of patients.

The efficacy of SARCLISA was established based upon progression-free survival (PFS). PFS results were assessed by an Independent Response Committee based on central laboratory data for M-protein and central radiologic imaging review using the International Myeloma Working Group (IMWG) criteria. The improvement in PFS represented a 40% reduction in the risk of disease progression or death in patients treated with Isa-VRd.

Efficacy results are presented in Table 12 and Kaplan-Meier curves for PFS are provided in Figure 3:

Table 12 – Efficacy Results of SARCLISA in combination with bortezomib, lenalidomide, and dexamethasone versus bortezomib, lenalidomide, and dexamethasone (IMROZ)
Endpoint | SARCLISA + bortezomib + lenalidomide + dexamethasone N =265 | Bortezomib + lenalidomide + dexamethasone N = 181
Progression-Free Survival [Based on ITT population.]
Median (months) [95% CI] | NR [NR–NR] | 54.34 [45.21–NR]
Hazard ratio [Stratified by age (<70 years vs ≥70 years) and Revised International Staging System (R-ISS) stage (I or II vs. III or not classified) according to IRT.] [95% CI] | 0.60 [0.44–0.81]
p-value (Stratified Log-Rank test) [A comparison is considered statistically significant if the p-value is <0.0148.] | 0.0009
Overall Response Rate [sCR, CR, VGPR, and PR were evaluated by the IRC using the IMWG response criteria.]
Responders (sCR+CR+VGPR+PR) N(%) [95% CI] [Estimated using Clopper-Pearson method.] | 242 (91) [87–94] | 167 (92) [87–96]
Stringent Complete Response (sCR) N(%) | 29 (11) | 10 (6)
Complete Response (CR) N(%) | 169 (64) | 106 (59)
Very Good Partial Response (VGPR) N(%) | 38 (14) | 34 (19)
Partial Response (PR) N(%) | 6 (2.3) | 17 (9)
CR or better (sCR and CR) [Other efficacy endpoints of CR and MRD negativity CR were tested hierarchically after PFS.] N(%) [95% CI] | 198 (75) [69–80] | 116 (64) [57–71]
p-value (Stratified Cochran-Mantel-Haenszel) | 0.0160
Minimal Residual Disease (MRD)
MRD negativity rate [Patients achieved both MRD negativity (threshold of 10^-5) and response of CR or better.] [Based on a sensitivity level of 10^-5 by the next-generation sequencing assay (clonoSEQ).] N(%) [95% CI] | 147 (55) [49–62] | 74 (41) [34–48]
p-value (Stratified Cochran-Mantel-Haenszel) | 0.0026
Number of patients with CR or better (sCR and CR) | 198 | 116
MRD negativity rate in patients with CR or better N(%) | 147 (74) [68–80] | 74 (64) [54–73]
[95% CI]
NR: not reached.
Median follow-up time=60 months.

Median overall survival was not reached for either treatment group. At a median follow-up time of 60 months, 26% of patients in the Isa-VRd group and 32.6% of patients in the VRd group had died (HR=0.78; 95% CI: 0.55 to 1.1).

Figure 3 – Kaplan-Meier Curves of PFS – ITT population – IMROZ

16 HOW SUPPLIED/STORAGE AND HANDLING

How Supplied

SARCLISA (isatuximab-irfc) injection is a clear to slightly opalescent, colorless to slightly yellow solution, essentially free of visible particulates, supplied as follows:

- One 100 mg/5 mL (20 mg/mL) single-dose vial in a carton: NDC 0024-0654-01
- One 500 mg/25 mL (20 mg/mL) single-dose vial in a carton: NDC 0024-0656-01

Storage

Store in a refrigerator at 36°F to 46°F (2°C to 8°C) in the original carton to protect from light. Do not freeze. Do not shake.

Handling and Disposal

Discard unused portion of solution. All materials that have been utilized for dilution and administration should be disposed of according to standard procedures.

17 PATIENT COUNSELING INFORMATION

Advise the patient to read the FDA-approved patient labeling (Patient Information).

Infusion-Related Reaction

Advise patients to seek immediate medical attention for any of the following signs and symptoms of infusion-related reactions: shortness of breath, wheezing or trouble breathing; swelling of the face, mouth, throat, or tongue; throat tightness; palpitations; dizziness, lightheadedness, or fainting; headache; cough; rash or itching; nausea; runny or stuffy nose; or chills [see Warnings and Precautions (5.1)].

Infections

Inform patients about the risk of developing infections during SARCLISA treatment, and to report immediately any fever or symptoms of infection to their healthcare provider [see Warnings and Precautions (5.2)].

Neutropenia

Inform patients about the risk of neutropenia and infection during SARCLISA treatment and the importance of reporting immediately any fever or symptoms of infection to their healthcare provider [see Warnings and Precautions (5.3) and Adverse Reactions (6.1)].

Second Primary Malignancies

Inform patients of the risk of developing second primary malignancies during treatment with SARCLISA when given with pomalidomide and dexamethasone or with carfilzomib and dexamethasone, or with bortezomib, lenalidomide, and dexamethasone [see Warnings and Precautions (5.4)].

Cardiac Toxicities

Inform patients about the risk of cardiac failure during treatment with SARCLISA when given with carfilzomib and dexamethasone, and the importance of reporting immediately any difficulty breathing, cough, or leg swelling to their healthcare provider [see Adverse Reactions (6.1)].

Interference with Laboratory Tests

Advise patients to inform healthcare providers and transfusion center personnel that they are treated with SARCLISA in case a red blood cell transfusion is planned. Advise patients that SARCLISA may affect the results of blood tests to match their blood type for approximately 6 months after their last infusion of SARCLISA [see Warnings and Precautions (5.5) and Drug Interactions (7.1)].

Embryo-Fetal Toxicity

Advise pregnant women and females of reproductive potential of the potential risk to a fetus and to use effective contraception during treatment and for 5 months after the last dose of SARCLISA [see Use in Specific Populations (8.1, 8.3)].

Advise patients that pomalidomide or lenalidomide have the potential to cause fetal harm and have specific requirements regarding contraception, pregnancy testing, blood and sperm donation, and transmission in sperm. Advise patients to report suspected or known pregnancies. Pomalidomide and lenalidomide are only available through a REMS program [see Use in Specific Populations (8.1, 8.3)].

Manufactured by:
sanofi-aventis U.S. LLC
Morristown, NJ 07960

A SANOFI COMPANY
U.S. License No. 1752

SARCLISA is a registered trademark of Sanofi

©2025 sanofi-aventis U.S. LLC

Patient Information
SARCLISA® (sar-cli-sa)
(isatuximab-irfc)
injection

SARCLISA is used together with two or three other combinations of medicines: either pomalidomide and dexamethasone, or carfilzomib and dexamethasone, or bortezomib, lenalidomide, and dexamethasone. You should also read the Medication Guide that comes with pomalidomide and lenalidomide. You can ask your healthcare provider or pharmacist for information about carfilzomib and dexamethasone.

What is SARCLISA?
SARCLISA is a prescription medicine used in combination with:

- the medicines pomalidomide and dexamethasone, to treat adults who have received at least 2 prior therapies including lenalidomide and a proteasome inhibitor to treat multiple myeloma.
- the medicines carfilzomib and dexamethasone, to treat adults with multiple myeloma who have already received 1 to 3 lines of treatment and they did not work or are no longer working.
- the medicines bortezomib, lenalidomide and dexamethasone, to treat adults with newly diagnosed multiple myeloma who cannot receive a type of stem cell transplant that uses their own stem cells (autologous stem cell transplant).

It is not known if SARCLISA is safe and effective in children.

Do not receive SARCLISA if you have a severe allergic reaction to isatuximab-irfc or any of the ingredients in SARCLISA. See the end of this leaflet for complete list of ingredients in SARCLISA.

Before receiving SARCLISA, tell your healthcare provider about all of your medical conditions, including if you:

- have an infection.
- have heart problems, if your healthcare provider prescribes SARCLISA in combination with carfilzomib and dexamethasone for you.
- have had shingles (herpes zoster).
- are pregnant or plan to become pregnant. SARCLISA can harm your unborn baby.
  - Females who are able to become pregnant should use an effective method of birth control during treatment and for 5 months after your last dose of SARCLISA. Talk to your healthcare provider about birth control methods that you can use during this time.
  - Tell your healthcare provider right away if you think you are pregnant or become pregnant during treatment with SARCLISA.
  - Before receiving SARCLISA in combination with either pomalidomide or lenalidomide, females and males must agree to the instructions in the pomalidomide or lenalidomide REMS programs. The pomalidomide and lenalidomide REMS programs have specific requirements about birth control, pregnancy testing, blood donation, and sperm donation that you need to know. Talk to your healthcare provider to learn more about pomalidomide or lenalidomide.
- are breastfeeding or plan to breastfeed. It is not known if SARCLISA passes into your breast milk. Do not breastfeed during treatment with SARCLISA.

Tell your healthcare provider about all the medicines you take, including prescription and over-the-counter medicines, vitamins, and herbal supplements.

How will I receive SARCLISA?

- SARCLISA will be given to you by your healthcare provider by intravenous (IV) infusion into your vein.
- SARCLISA in combination with pomalidomide and dexamethasone, or SARCLISA in combination with carfilzomib and dexamethasone is given in treatment cycles of 28 days (4 weeks).
  - Cycle 1 (28-day cycle), SARCLISA is given weekly.
  - Cycle 2 and beyond (28-day cycles), SARCLISA is given every 2 weeks.
- SARCLISA in combination with bortezomib, lenalidomide, and dexamethasone is given in treatment cycles of 42 days (6 weeks) from cycle 1 to 4 and in treatment cycles of 28 days (4 weeks) from cycle 5.
  - Cycle 1 (42-day cycle), SARCLISA is given weekly (Days 1, 8, 15, 22, and 29).
  - Cycles 2 to 4 (42-day cycles), SARCLISA is given every 2 weeks (Days 1, 15, and 29).
  - Cycles 5 to 17 (28-day cycles), SARCLISA is given every 2 weeks (Days 1 and 15).
  - Cycles 18 and beyond (28-day cycles), SARCLISA is given every 4 weeks.
- Your healthcare provider will decide how many treatments you will receive.
- Your healthcare provider will give you medicines before each infusion of SARCLISA, to help reduce the risk of infusion reactions (make them less frequent and severe).
- If you miss any appointments, call your healthcare provider as soon as possible to reschedule your appointment.

What are the possible side effects of SARCLISA?
SARCLISA may cause serious side effects including:

- Infusion reactions. Infusion reactions are common with SARCLISA and can sometimes be severe or life threatening.
  - Your healthcare provider will prescribe medicines before each infusion of SARCLISA to help decrease your risk for infusion reactions or to help make any infusion reaction less severe. You will be monitored for infusion reactions during each infusion of SARCLISA.
  - Your healthcare provider may slow down or stop your infusion, or completely stop treatment with SARCLISA if you have an infusion reaction.
  Get medical help right away if you develop any of the following symptoms of infusion reaction during or after an infusion of SARCLISA:

- shortness of breath, wheezing or trouble breathing
- swelling of the face, mouth, throat, or tongue
- throat tightness
- palpitations

- dizziness, lightheadedness, or fainting
- headache
- cough
- rash or itching

- nausea
- runny or stuffy nose
- chills

- Infections. SARCLISA can cause infections that are severe, life-threatening, or that may lead to death. Your healthcare provider will monitor you for signs and symptoms of infection before and during treatment with SARCLISA. Your healthcare provider may prescribe medicines for you to help prevent infections and treat you as needed if you develop an infection during treatment with SARCLISA. Tell your healthcare provider right away if you develop a fever or any signs or symptoms of infection during treatment with SARCLISA.
  - Decreased white blood cell counts. Decreased white blood cell counts are common with SARCLISA and certain white blood cells can be severely decreased. Fever can occur with low white blood cell counts and may be a sign that you have an infection. Your healthcare provider will check your blood cell counts during treatment with SARCLISA and may prescribe a medicine to help increase your white blood cell counts. Tell your healthcare provider right away if you develop any fever or symptoms of infection during treatment with SARCLISA.
- Risk of new cancers. New cancers have happened in people during and after treatment with SARCLISA. Your healthcare provider will monitor you for new cancers during treatment with SARCLISA.
- Changes in blood tests. SARCLISA may affect the results of blood tests to match your blood type for about 6 months after your last infusion of SARCLISA. Your healthcare provider will do blood tests to match your blood type before you start treatment with SARCLISA. Tell all of your healthcare providers that you are being treated with SARCLISA before receiving blood transfusions.

The most common side effects of SARCLISA in combination with pomalidomide and dexamethasone include:

- upper respiratory tract infection
- lung infection (pneumonia)
- diarrhea

- decreased red blood cell count (anemia)
- decreased platelet count (thrombocytopenia)

The most common side effects of SARCLISA in combination with carfilzomib and dexamethasone include:

- upper respiratory tract infection
- tiredness and weakness
- high blood pressure
- diarrhea
- lung infection (pneumonia)
- trouble breathing

- trouble sleeping
- bronchitis
- cough
- back pain
- decreased red blood cell count (anemia)
- decreased platelet count (thrombocytopenia)

The most common side effects of SARCLISA in combination with bortezomib, lenalidomide and dexamethasone include:

- upper respiratory tract infection
- diarrhea
- tiredness and weakness
- tingling or numbness of the arms or legs
- lung infection (pneumonia)
- muscle or bone pain
- clouding of your eye (cataract)

- constipation
- swelling of the hands, legs, ankles and feet
- rash
- trouble sleeping
- COVID-19
- decreased red blood cell count (anemia)
- decreased platelet count (thrombocytopenia)

Heart failure can happen during treatment with SARCLISA in combination with carfilzomib and dexamethasone. Tell your healthcare provider right away if you develop any of the following symptoms:

- trouble breathing

- cough

- swelling of your ankles, feet, and legs

These are not all the possible side effects of SARCLISA. For more information, ask your healthcare provider or pharmacist.

Call your doctor for medical advice about side effects. You may report side effects to FDA at 1-800-FDA-1088.

General information about the safe and effective use of SARCLISA.
Medicines are sometimes prescribed for purposes other than those listed in a Patient Information leaflet. You can ask your pharmacist or healthcare provider for information about SARCLISA that is written for health professionals.

What are the ingredients in SARCLISA?
Active ingredient: isatuximab-irfc
Inactive ingredients: histidine, histidine hydrochloride monohydrate, polysorbate 80, sucrose, and water for injection.
Manufactured by: sanofi-aventis U.S. LLC, Morristown, NJ 07960, A SANOFI COMPANY. U.S. License No. 1752.
SARCLISA is a registered trademark of Sanofi. ©2025 sanofi-aventis U.S. LLC.
For more information, go to www.sanofi-aventis.us or call 1-800-633-1610.

This Patient Information has been approved by the U.S. Food and Drug Administration.

Revised: 06/2025

PRINCIPAL DISPLAY PANEL - 100 mg/5 mL Vial Carton

NDC 0024-0654-01
Rx only

SARCLISA®
(isatuximab-irfc)
Injection

100 mg/5 mL (20 mg/mL)

For Intravenous Infusion After Dilution

One single-dose vial
Discard unused portion

sanofi

PRINCIPAL DISPLAY PANEL - 500 mg/25 mL Vial Carton

NDC 0024-0656-01
Rx only

SARCLISA®
(isatuximab-irfc)
Injection

500 mg/25 mL (20 mg/mL)

For Intravenous Infusion After Dilution

One single-dose vial
Discard unused portion

sanofi